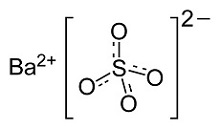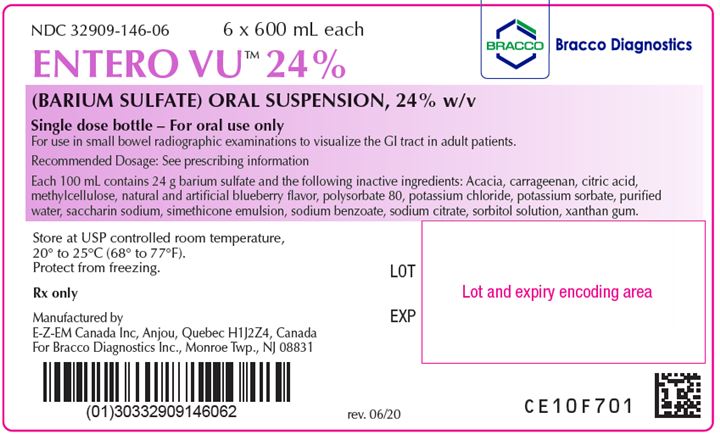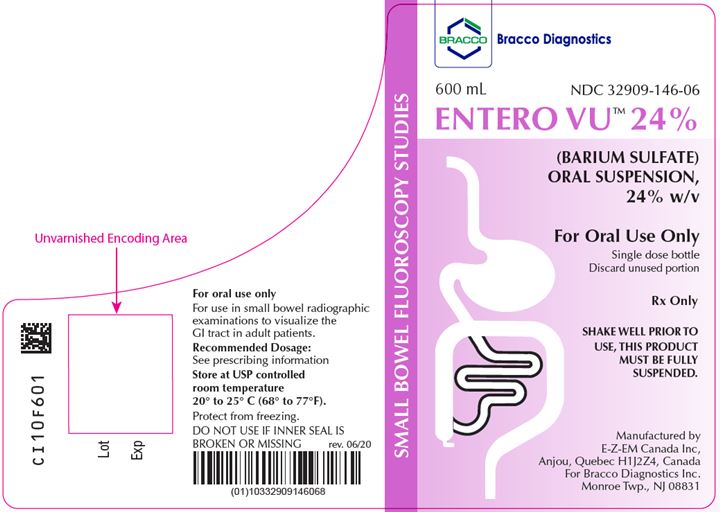 DRUG LABEL: ENTERO Vu 24%
NDC: 32909-145 | Form: SUSPENSION
Manufacturer: E-Z-EM Canada Inc
Category: prescription | Type: HUMAN PRESCRIPTION DRUG LABEL
Date: 20220117

ACTIVE INGREDIENTS: BARIUM SULFATE 240 mg/1 mL
INACTIVE INGREDIENTS: ACACIA; ANHYDROUS CITRIC ACID; CARRAGEENAN SODIUM; DIMETHICONE 350; DIMETHICONE 1000; METHYLCELLULOSE (400 MPA.S); POLYSORBATE 80; POTASSIUM CHLORIDE; POTASSIUM SORBATE; SACCHARIN SODIUM; SILICON DIOXIDE; SODIUM BENZOATE; SORBITOL; TRISODIUM CITRATE DIHYDRATE; WATER; XANTHAN GUM

HIGHLIGHTS OF PRESCRIBING INFORMATION

These highlights do not include all the information needed to use ENTERO VU 24% safely and effectively. See full prescribing information for ENTERO VU 24%.
ENTERO VU 24% (barium sulfate) oral suspension
Initial U.S. Approval: 2016

1 INDICATIONS AND USAGE

ENTERO VU 24% is a radiographic contrast agent indicated for use in small bowel radiographic examinations to visualize the gastrointestinal (GI) tract in adult patients (1)

2 DOSAGE AND ADMINISTRATION

- For oral use only:
  - Adults: Recommended dose is 600 mL (2.1)

3 DOSAGE FORMS AND STRENGTHS

- Oral Suspension: barium sulfate (24% w/v) supplied in single dose bottle (3)

4 CONTRAINDICATIONS

- Known or suspected perforation of the gastrointestinal (GI) tract (4)
- Known obstruction of the GI tract (4)
- Conditions associated with high risk of GI perforation or aspiration (4)
- Known hypersensitivity to barium sulfate or any of the excipients of ENTERO VU 24% (4)

5 WARNINGS AND PRECAUTIONS

- Hypersensitivity reactions: Emergency equipment and trained personnel should be immediately available (5.1)
- Intra-abdominal barium leakage: May occur in conditions such as GI fistula, ulcer, inflammatory bowel disease, appendicitis, diverticulitis, severe stenosis or obstructing lesions of the GI tract (5.2)
- Delayed GI transit and obstruction: Patients should maintain adequate hydration in days following barium sulfate procedure to avoid obstruction or impaction (5.3)
- Aspiration Pneumonitis: Patients with a history of food aspiration or with swallowing disorders are at increased risk. Monitor patients for aspiration (5.4)

6 ADVERSE REACTIONS

Common adverse reactions include nausea, vomiting, diarrhea and abdominal cramping (6)

To report SUSPECTED ADVERSE REACTIONS, contact Bracco Diagnostics Inc at 1-800-257-5181 or FDA at 1-800-FDA-1088 or www.fda.gov/medwatch

FULL PRESCRIBING INFORMATION

1 INDICATIONS AND USAGE

ENTERO VU 24% is indicated for use in small bowel radiographic examinations to visualize the gastrointestinal (GI) tract in adult patients.

2 DOSAGE AND ADMINISTRATION

2.1 Recommended Dosing

- The recommended oral dose of ENTERO VU 24% is:
  - Adults: 600 mL

2.2 Administration Instructions

- For oral use only
- Shake bottle vigorously prior to oral administration to fully suspend product
- Administer undiluted
- Discard any unused suspension
- Advise patients to hydrate following the barium sulfate procedure
- Advise patient at risk for constipation or delayed gastrointestinal transit to monitor for worsening of their condition after administration of barium sulfate and seek medical attention if worsening and advise using laxatives to enhance gastrointestinal transit.

3 DOSAGE FORMS AND STRENGTHS

Oral suspension: barium sulfate (24% w/v) supplied in a single-dose white HDPE plastic bottle as a ready-to-use suspension for oral administration. Each bottle contains 600 mL of suspension.

4 CONTRAINDICATIONS

ENTERO VU 24% is contraindicated in patients with the following conditions:

- known or suspected perforation of the GI tract
- known obstruction of the GI tract
- high risk of GI perforation such as those with a recent GI perforation, acute GI hemorrhage or ischemia, toxic megacolon, severe ileus, post GI surgery or biopsy, acute GI injury or burn, or recent radiotherapy to the pelvis
- high risk of aspiration such as those with known or suspected tracheo-esophageal fistula or obtundation
- known severe hypersensitivity to barium sulfate or any of the excipients of ENTERO VU 24%

5 WARNINGS AND PRECAUTIONS

5.1 Hypersensitivity Reactions

Barium sulfate preparations contain a number of excipients, including natural and artificial flavors and may induce serious hypersensitivity reactions. The manifestations include hypotension, bronchospasm and other respiratory impairments, and dermal reactions including rashes, urticaria and itching. A history of bronchial asthma, atopy, food allergies, or a previous reaction to a contrast agent may increase the risk for hypersensitivity reactions. Emergency equipment and trained personnel should be immediately available for treatment of a hypersensitivity reaction.

5.2 Intra-abdominal Barium Leakage

The use of ENTERO VU 24% is contraindicated in patients at high risk of perforation of the GI tract [see Contraindications (4)]. Administration of ENTERO VU 24% may result in leakage of barium from the GI tract in the presence of conditions that increase the risk of perforation such as known carcinomas, GI fistula, inflammatory bowel disease, gastric or duodenal ulcer, appendicitis, diverticulitis, and in patients with a severe stenosis at any level of the GI tract, especially if it is distal to the stomach. Barium leakage has been associated with peritonitis and granuloma formation.

5.3 Delayed Gastrointestinal Transit and Obstruction

Orally administered barium sulfate may accumulate proximal to a constricting lesion of the colon, causing obstruction or impaction with development of baroliths (inspissated barium associated with feces) and may cause abdominal pain, appendicitis, bowel obstruction, or perforation. Patients with the following conditions are at higher risk for developing obstruction or baroliths: severe stenosis at any level of the GI tract, impaired GI motility, electrolyte imbalance, dehydration, on a low residue diet, on medications that delay GI motility, constipation, and the elderly [see Use in Specific Populations (8.5)]. To reduce the risk of delayed GI transit and obstruction, patients should maintain adequate hydration after the barium sulfate procedure.

5.4 Aspiration Pneumonitis

The use of ENTERO VU 24% is contraindicated in patients with trachea-esophageal fistula [see Contraindications (4)]. Oral administration of barium is associated with aspiration pneumonitis, especially in patients with a history of food aspiration or with compromised swallowing mechanism. Vomiting following oral administration of barium sulfate may lead to aspiration pneumonitis. In patients at risk for aspiration, begin the procedure with a small ingested volume of ENTERO VU 24%. Monitor the patient closely for aspiration, discontinue administration of ENTERO VU 24% if aspiration is suspected, and monitor for development of aspiration pneumonitis.

5.5 Systemic Embolization

Barium sulfate products may occasionally intravasate into the venous drainage of the large bowel and enter the circulation as a "barium embolus" leading to potentially fatal complications which include systemic and pulmonary embolism, disseminated intravascular coagulation, septicemia and prolonged severe hypotension. Although this complication is uncommon after oral administration of a barium sulfate suspension, monitor patients for potential intravasation when administering barium sulfate.

5.6 Risk with Hereditary Fructose Intolerance

ENTERO VU 24% contains sorbitol which may cause severe symptoms if ingested by patients with hereditary fructose intolerance. Severe symptoms may include the following: vomiting, hypoglycemia, jaundice, hemorrhage, hepatomegaly, hyperuricemia, and kidney failure. Before administration of ENTERO VU 24% assess patients for a history of hereditary fructose intolerance and avoid use in these patients.

6 ADVERSE REACTIONS

The following adverse reactions have been identified from spontaneous reporting or clinical studies of barium sulfate administered orally. Because the reactions are reported voluntarily from a population of uncertain size, it is not always possible to reliably estimate their frequency or to establish a causal relationship to drug exposure:

- Nausea, vomiting, diarrhea and abdominal cramping
- Serious adverse reactions and fatalities include aspiration pneumonitis, barium sulfate impaction, intestinal perforation with consequent peritonitis and granuloma formation, vasovagal and syncopal episodes

8 USE IN SPECIFIC POPULATIONS

8.1 Pregnancy

Risk Summary

ENTERO VU 24% is not absorbed systemically following oral administration, and maternal use is not expected to result in fetal exposure to the drug.

8.2 Lactation

Risk Summary

ENTERO VU 24% is not absorbed systemically by the mother following oral administration, and breastfeeding is not expected to result in exposure of the infant to the drug.

8.4 Pediatric Use

ENTERO VU 24% is not indicated for pediatric use.

8.5 Geriatric Use

Clinical studies of ENTERO VU 24% did not include sufficient numbers of subjects aged 65 and over to determine whether they respond differently from younger subjects. Other reported clinical experience has not identified differences in responses between the elderly and younger patients. In general, dose selection for an elderly patient should be cautious, usually starting at the low end of the dosing range, reflecting the greater frequency of decreased hepatic, renal, or cardiac function, and of concomitant disease or other drug therapy.

11 DESCRIPTION

ENTERO VU 24% (barium sulfate) is a radiographic contrast agent that is supplied as a suspension (24% w/v) for oral administration. The active ingredient barium sulfate is designated chemically as BaSO4 with a molecular weight of 233.4 g/mol, a density of 4.5 g/cm^3, and the following chemical structure

ENTERO VU 24% contains the following excipients: acacia, carrageenan, citric acid, methylcellulose, natural and artificial blueberry flavor, polysorbate 80, potassium chloride, potassium sorbate, purified water, saccharin sodium, simethicone emulsion, sodium benzoate, sodium citrate, sorbitol solution, and xanthan gum.

12 CLINICAL PHARMACOLOGY

12.1 Mechanism of Action

Due to its high atomic number, barium (the active ingredient in ENTERO VU 24%) is opaque to x-rays and therefore acts as a positive contrast agent for radiographic studies.

12.2 Pharmacodynamics

Barium sulfate is biologically inert and has no known pharmacological effects.

12.3 Pharmacokinetics

Under physiological conditions, barium sulfate passes through the gastrointestinal tract in an unchanged form and is absorbed only in small, pharmacologically insignificant amounts.

13 NONCLINICAL TOXICOLOGY

13.1 Carcinogenesis, Mutagenesis, Impairment of Fertility

No animal studies have been performed to evaluate the carcinogenic potential of barium sulfate or potential effects on fertility.

16 HOW SUPPLIED/STORAGE AND HANDLING

16.1 How Supplied

ENTERO VU 24% (barium sulfate) is supplied as a suspension (24% w/v) in a single-dose HDPE plastic bottle containing 600 mL of barium sulfate suspension (24% w/v).

Provided as: 6 x 600 mL bottles (NDC 32909-146-06)

16.2 Storage and Handling

Store at USP controlled room temperature 20°C to 25°C (68°F to 77° F). Protect from freezing.

17 PATIENT COUNSELING INFORMATION

After administration, advise patients to:

- Maintain adequate hydration [see Dosage and Administration (2.2) and Warnings and Precautions (5.3)].
- Seek medical attention for worsening of constipation or slow gastrointestinal passage [see Warnings and Precautions (5.3)].
- Seek medical attention for any delayed onset of hypersensitivity: rash, urticaria, or respiratory difficulty [see Warnings and Precautions (5.1)].

Rx only

Manufactured by
EZEM Canada Inc
Anjou (Quebec) Canada H1J 2Z4

For
Bracco Diagnostics Inc.
Monroe Township, NJ 08831

CL10F501

rev.06/20

Entero Vu™ 24% - 600 ml - Inner Package
Barium Sulfate Suspension
NDC: 32909-146-06

Entero Vu™ 24% - 600 ml - Outer Package
Barium Sulfate Suspension
NDC: 32909-146-06